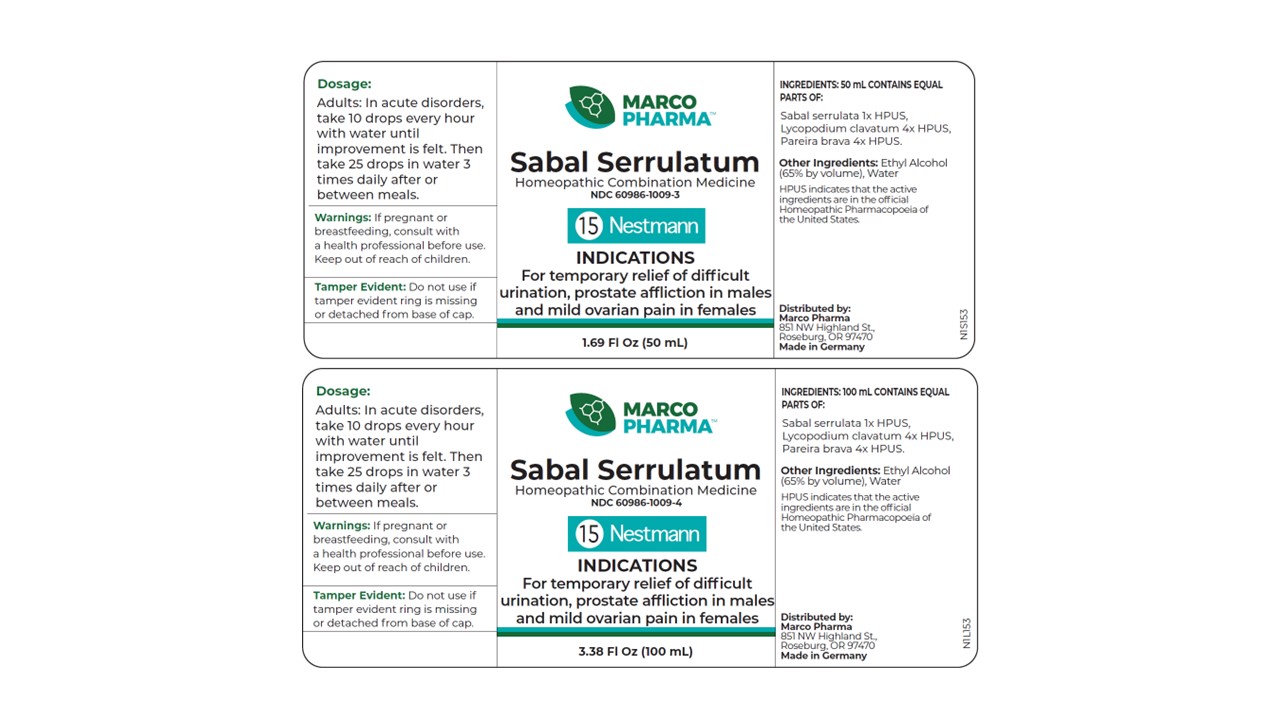 DRUG LABEL: Sabal Serrulatum
NDC: 60986-1009 | Form: LIQUID
Manufacturer: Marco Pharma International LLC.
Category: homeopathic | Type: HUMAN OTC DRUG LABEL
Date: 20260112

ACTIVE INGREDIENTS: SAW PALMETTO 1 [hp_X]/100 mL; LYCOPODIUM CLAVATUM SPORE 4 [hp_X]/100 mL; CHONDRODENDRON TOMENTOSUM ROOT 4 [hp_X]/100 mL
INACTIVE INGREDIENTS: WATER; ALCOHOL

Drug Facts

Active Ingredients

Saw Palmetto 1xHPUS

Club Moss 4xHPUS

Pareira 4xHPUS

The letters HPUS indicates that the components in this product are officially monographed in the Homeopathic Pharmacopoeia of United Sates.

Purpose

For relief of difficult urination; prostate afflictions.

Keep out of reach of children.

Suggested use

In acute disorders, take 10 drops in pure water every hour until improvement is felt. Then take 25 drops in pure water three times daily after or between meals.

Warnings

If pregnant or breast-feeding, consult a health professional before use.

DOSAGE AND ADMINISTRATION

(Read Suggested Use Section)

Inactive Ingredients

Ethyl alcohol (65% by vol.) and water.